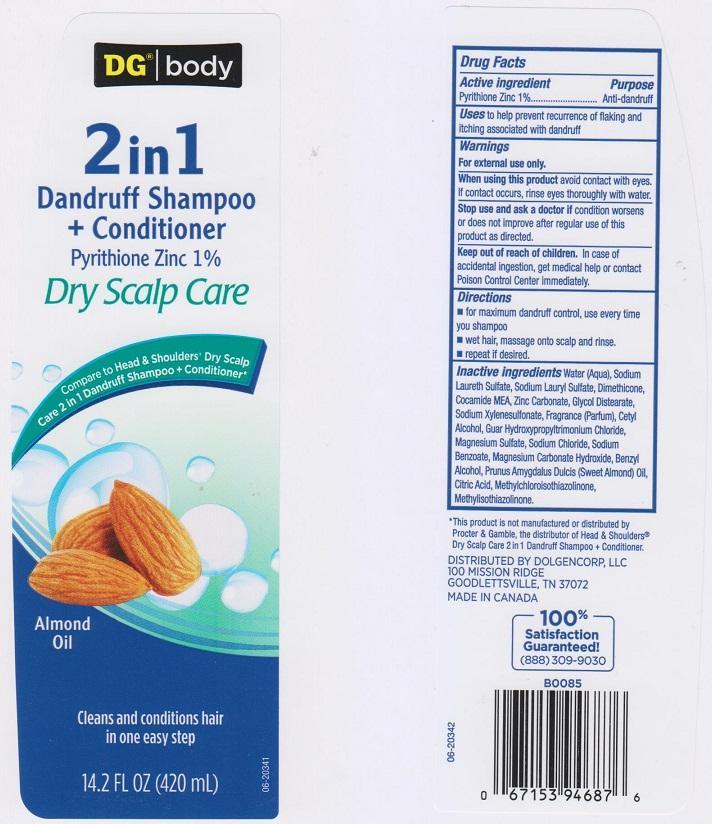 DRUG LABEL: DG BODY
NDC: 55910-425 | Form: LIQUID
Manufacturer: DOLGENCORP INC
Category: otc | Type: HUMAN OTC DRUG LABEL
Date: 20150429

ACTIVE INGREDIENTS: PYRITHIONE ZINC 10 mg/1 mL
INACTIVE INGREDIENTS: WATER; SODIUM LAURETH SULFATE; SODIUM LAURYL SULFATE; DIMETHICONE; COCO MONOETHANOLAMIDE; ZINC CARBONATE; GLYCOL DISTEARATE; SODIUM XYLENESULFONATE; CETYL ALCOHOL; GUAR HYDROXYPROPYLTRIMONIUM CHLORIDE (1.7 SUBSTITUENTS PER SACCHARIDE); MAGNESIUM SULFATE; SODIUM CHLORIDE; SODIUM BENZOATE; MAGNESIUM CARBONATE HYDROXIDE; BENZYL ALCOHOL; ALMOND OIL; CITRIC ACID MONOHYDRATE; METHYLCHLOROISOTHIAZOLINONE; METHYLISOTHIAZOLINONE

DRUG FACTS

ACTIVE INGREDIENT

PYRITHIONE ZINC 1%

PURPOSE

ANTI-DANDRUFF

USES

TO HELP PREVENT RECURRENCE OF FLAKING AND ITCHING ASSOCIATED WITH DANDRUFF

WARNINGS

FOR EXTERNAL USE ONLY

WHEN USING THIS PRODUCT

AVOID CONTACT WITH EYES. IF CONTACT OCCURS, RINSE EYES THOROUGHLY WITH WATER

STOP USE AND ASK A DOCTOR IF

CONDITION WORSENS OR DOES NOT IMPROVE AFTER REGULAR USE OF THIS PRODUCT AS DIRECTED

KEEP OUT OF REACH OF CHILDREN

IN CASE OF ACCIDENTAL INGESTION, GET MEDICAL HELP OR CONTACT A POISON CONTROL CENTER IMMEDIATELY

DIRECTIONS

- FOR MAXIMUM DANDRUFF CONTROL, USE EVERY TIME YOU SHAMPOO
- WE HAIR, MASSAGE ONTO SCALP AND RINSE
- REPEAT IF DESIRED

INACTIVE INGREDIENTS

WATER (AQUA), SODIUM LAURETH SULFATE, SODIUM LAURYL SULFATE, DIMETHICONE, COCAMDIE MEA, ZINC CARBONATE, GLYCOL DISTEARATE, SODIUM XYLENESULFONATE, FRAGRANCE (PARFUM), CETYL ALCOHOL, GUAR HYDROXYPROPYLTRIMONIUM CHLORIDE, MAGNESIUM SULFATE, SODIUM CHLORIDE, SODIUM BENZOATE, MAGNESIUM CARBONATE HYDROXIDE, BENZYL ALCOHOL, PRUNUS AMYGDALUS DULCIS (SWEET ALMOND) OIL, CITRIC ACID, METHYLCHLOROISOTHIAZOLINONE, METHYLISOTHIAZOLINONE